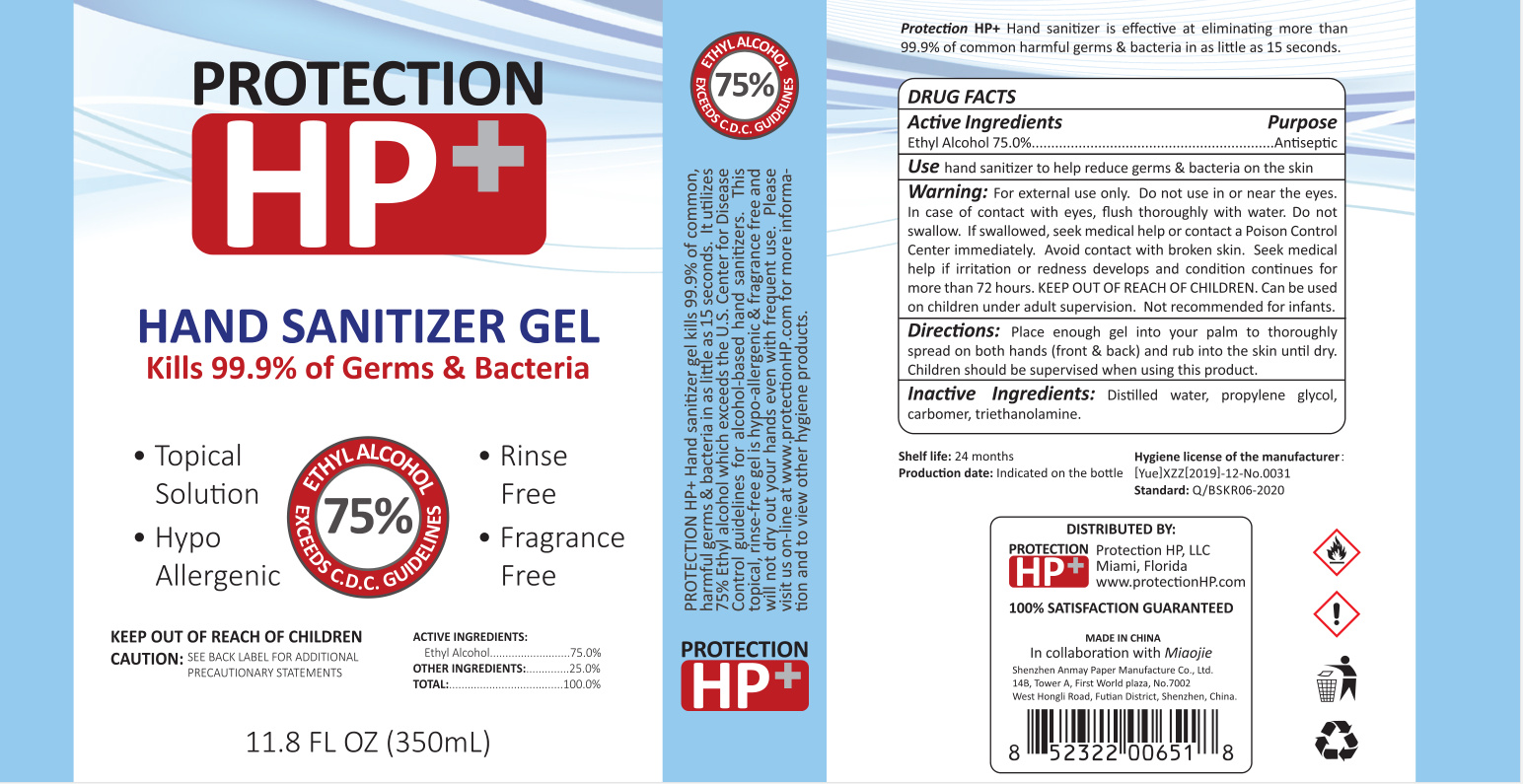 DRUG LABEL: PROTECTION HP HAND SANITIZERGEL
NDC: 54306-004 | Form: GEL
Manufacturer: Shenzhen Anmay Paper Manufacture Co., Ltd.
Category: otc | Type: HUMAN OTC DRUG LABEL
Date: 20200710

ACTIVE INGREDIENTS: PROPYLENE GLYCOL 0.35 g/350 mL; ALCOHOL 262.5 mL/350 mL; CARBOMER HOMOPOLYMER, UNSPECIFIED TYPE 1.05 g/350 mL; TROLAMINE 0.98 g/350 mL
INACTIVE INGREDIENTS: WATER

DOSAGE AND ADMINISTRATION

Store in a cool and dry place

INACTIVE INGREDIENT

Water

INDICATIONS AND USAGE

Place enough gel into your palm to thoroughly spread on both hands (front & back) and rub into the skin until dry.Children should be supervised when using this product.

ACTIVE INGREDIENT

carbomer

triethanolamine

ethanol

keep out of reach of children

PURPOSE

Disinfection
Sterilization
No Rinseing

WARNINGS

For external use only. Do not use in or near the eyes.In case of contact with eyes, flush thoroughly with water. Do not swallow. If swallowed, seek medical help or contact a Poison Control Center immediately. Avoid contact with broken skin. Seek medical help if iritation or redness develops and condition continues for more than 72 hours. KEEP OUT OF REACH OF CHILDREN. Can be used
on children under adult supervision. Not recommended for infants.